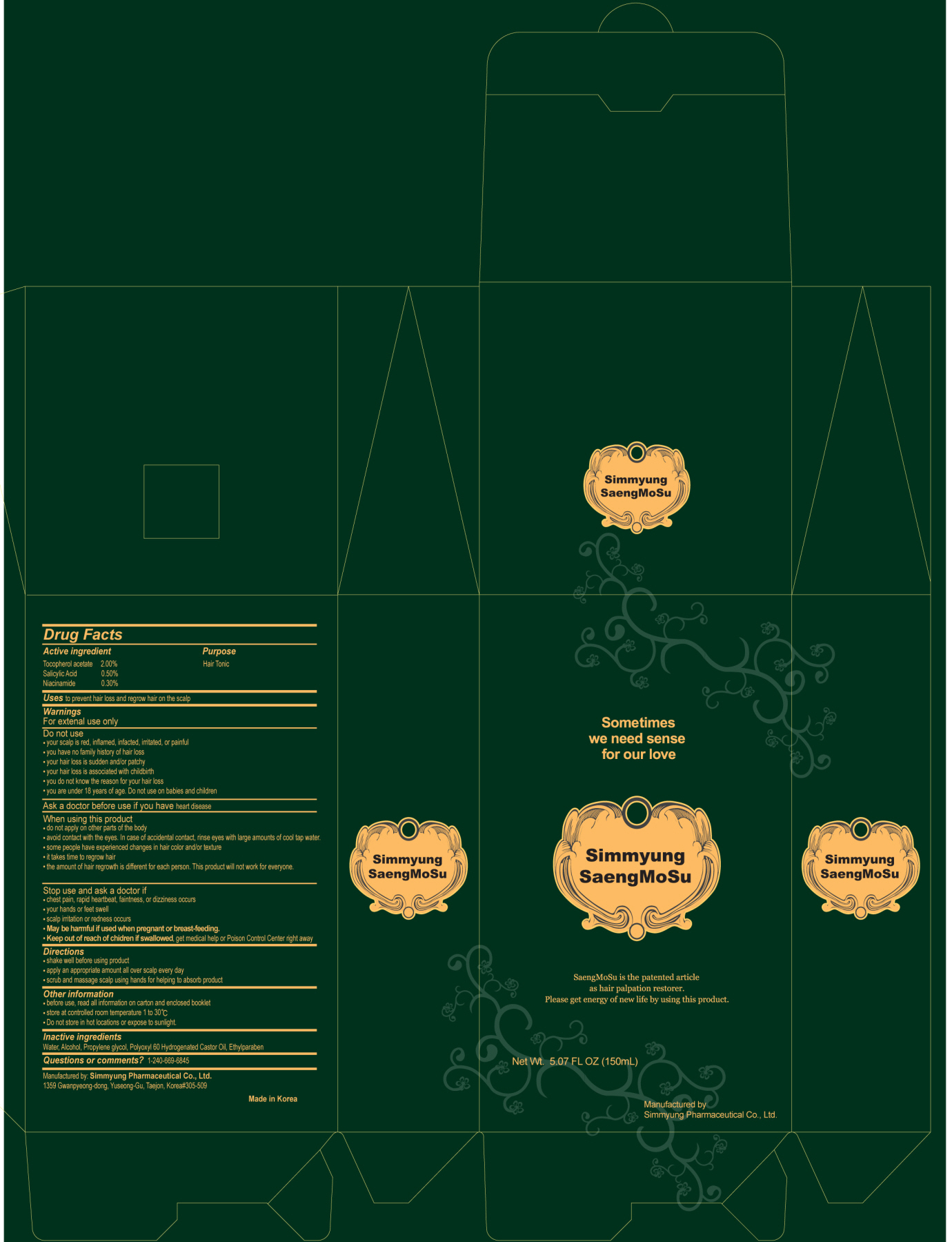 DRUG LABEL: SimmyungSaengMoSu
NDC: 32819-1001 | Form: LIQUID
Manufacturer: Simmyung Pharmaceutical Co Ltd
Category: otc | Type: HUMAN OTC DRUG LABEL
Date: 20101004

ACTIVE INGREDIENTS: ALPHA-TOCOPHEROL ACETATE 3 mL/150 mL; SALICYLIC ACID 0.75 mL/150 mL; NIACINAMIDE 0.45 mL/150 mL
INACTIVE INGREDIENTS: WATER; ALCOHOL; PROPYLENE GLYCOL; POLYOXYL 60 HYDROGENATED CASTOR OIL; ETHYLPARABEN

SimmyungSaengMoSu

Drug Facts

Active Ingredient
Tocopherol Acetate 2.00%
Salicylic Acid 0.50%
Niacinamide 0.30%

Purpose

Hair Tonic

Keep out of Reach of Children

Stop use and ask a doctor if
- chest pain, rapid heartbeat, faintness or dizziness occurs
- your hands or feet swell
- scalp irritation or redness occurs
- May be harmful if used when pregnant or breast-feeding.
- Keep out of reach of children if swallowed, get medical help or Poison Control Center right away

Indication & Usage

When using this product
- do not apply on other parts of the body
- avoid contact with the eyes. In case of accidental contact, rinse eyes with large amounts of cool tap water.
- some people have experienced changes in hair color and/or texture
- it takes time to regrow hair
- the amount of hair regrowth is different for each person. This product will not
work for everyone.

Warnings

For external use only
Do not use
- your scalp is red, inflamed, infected, irritated, or painful
- you have no family history of hair loss
- your hair loss is sudden and/or patchy
- your hair loss is associated with childbirth
- you do not know the reason for your hair loss
- you are under 18 years of age. Do not use on babies and children Ask adoctor before use if you have heart disease

Dosage & Administraion

- shake well before using product
- apply an appropriate amount all over scalp every day
- scrub and massage scalp using hands for helping to absorb product
Other information
- before use, read all information on carton and enclosed booklet
- store at controlled room temperature 1 to 30??br/>
- Do not store in hot locations or expose to sunlight

Inactive Ingredient

Water, Alcohol, Propylene glycol, Polyoxyl 60 hydrogenated Castor Oil, Ethylparaben

SimmyungSaengMoSu

Net WT. 5.07 FL OZ (150mL)